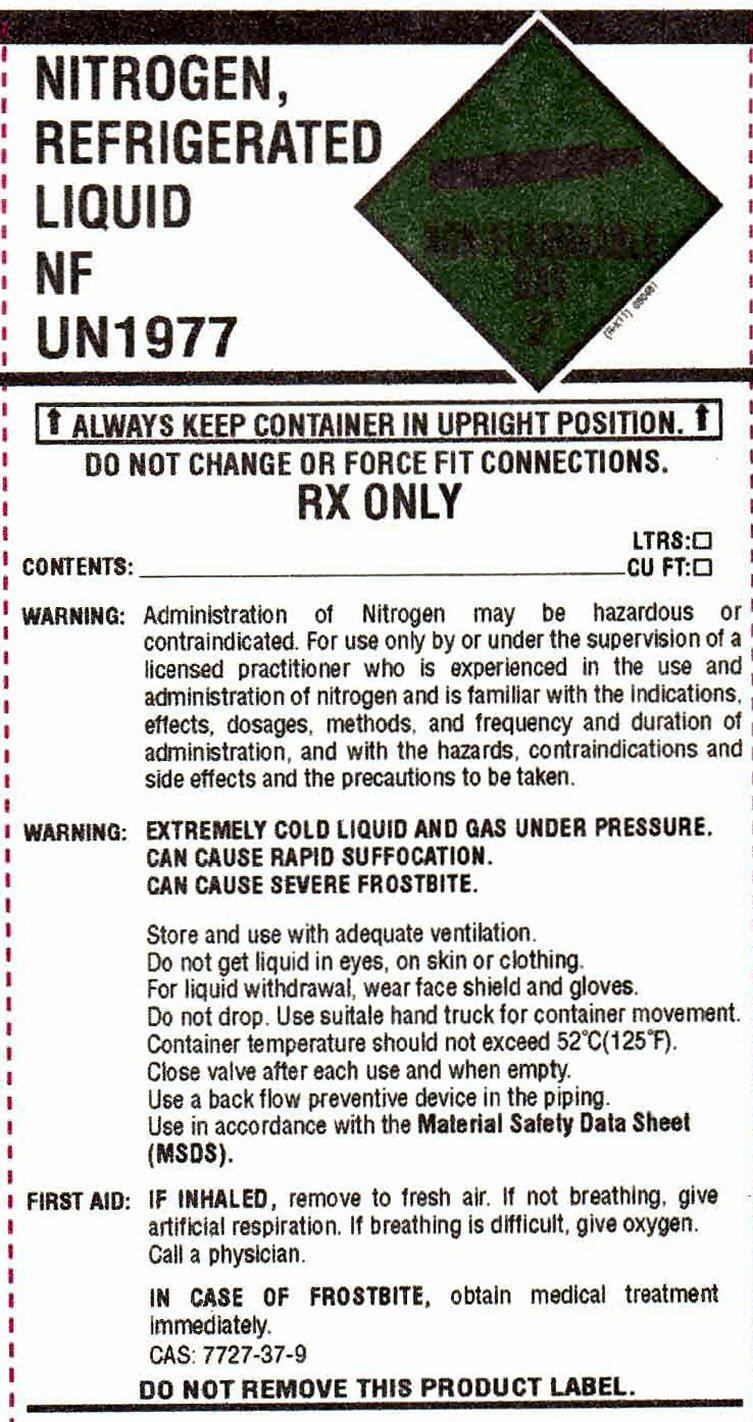 DRUG LABEL: NITROGEN
NDC: 65919-002 | Form: GAS
Manufacturer: Clinical 1 Home Medical, Inc.
Category: prescription | Type: HUMAN PRESCRIPTION DRUG LABEL
Date: 20251028

ACTIVE INGREDIENTS: NITROGEN 99 L/100 L

Nitrogen

Nitrogen Liquid Label

NITROGEN, REFRIGERATED LIQUID NF UN1977 NON-FLAMMABLE GAS 2

ALWAYS KEEP CONTAINER IN UPRIGHT POSITION

DO NOT CHANGE OR FORCE FIT CONNECTIONS.

RX ONLY LTRS:

CONTENTS:________________________________ CU FT:

WARNING: Administration of Nitrogen may be hazardous or contraindicated. For use only by or under the supervision of a licensed practitioner who is experienced in the use and administration of nitrogen and is familiar with the indications, effects, dosages, methods, and frequency and duration of administration, and with the hazards, contraindications and side effects and the precautions to be taken.

WARNING: EXTREMELY COLD LIQUID AND GAS UNDER PRESSURE.

CAN CAUSE RAPID SUFFOCATION.

CAN CAUSE SEVERE FROSTBITE.

Store and use with adequate ventilation.

Do not get liquid in eyes, on skin or clothing.

For liquid withdraw, wear face shield and gloves.

Do not drop. Use suitale hand truck for container movement.

Container temperature should not exceed 52 degrees C (125 degrees F).

Close valve after each use and when empty.

Use a back flow preventive device in the piping.

Use in accordance with the Material Safety Data Sheet (MSDS).

FIRST AID: IF INHALED, remove to fresh air. If not breathing, give artificial respiration. If breathing is difficult, give oxygen.

Call a physician.

IN CASE OF FROSTBITE, obtain medical treatment immediately.

CAS: 7727-37-9

DO NOT REMOVE THIS PRODUCT LABEL